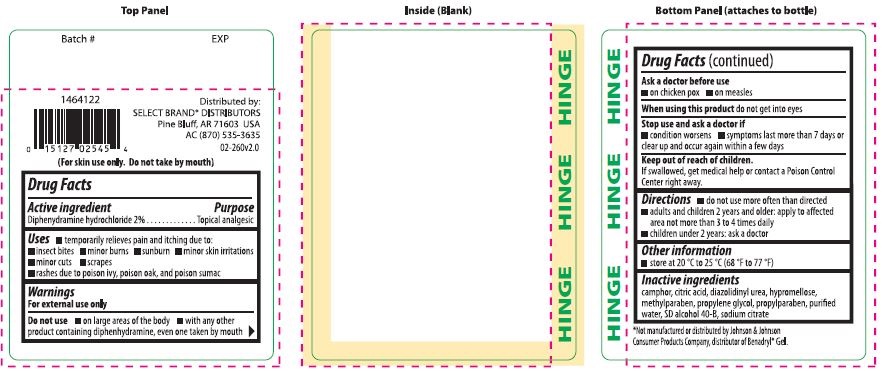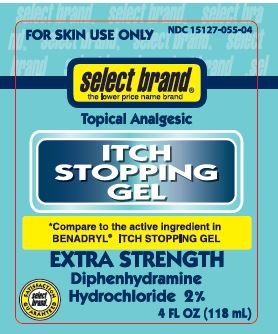 DRUG LABEL: Select Brand Extra Strength Itch Stopping
NDC: 15127-055 | Form: GEL
Manufacturer: Select Brand
Category: otc | Type: HUMAN OTC DRUG LABEL
Date: 20150108

ACTIVE INGREDIENTS: DIPHENHYDRAMINE HYDROCHLORIDE .2 g/10 mL
INACTIVE INGREDIENTS: CITRIC ACID MONOHYDRATE; DIAZOLIDINYL UREA; HYPROMELLOSES; METHYLPARABEN; PROPYLENE GLYCOL; PROPYLPARABEN; WATER; SODIUM CITRATE; ALCOHOL; CAMPHOR (SYNTHETIC)

Extra Strength
SELECT BRAND ITCH STOPPING GEL

Drug Facts

Active ingredient

Diphenhydramine HCl 2%

Purpose

Topical analgesic

Uses

- temporarily relieves pain and itching associated with:
  - insect bites
  - minor burns
  - sunburn
  - minor skin irritations
  - minor cuts
  - scrapes
  - rashes due to poison ivy, poison oak, and poison sumac

Warnings

For external use only.

Do not use

- on large areas of the body
- with any other product containing diphenhydramine, even one taken by mouth

Ask a doctor before use

- on chicken pox
- on measles

When using this product do not get into eyes

Stop use and ask a doctor if

- condition worsens
- symptoms persist for more than 7 days or clear up and occur again within a few days

Keep out of reach of children. If swallowed, get medical help or contact a Poison Control Center right away.

Directions

- do not use more than directed
- adults and children 2 years of age and older: apply to affected area not more than 3 to 4 times daily
- children under 2 years of age: ask a doctor

Other information

- store at 20oC to 25oC (68oF to 77oF)

Inactive ingredients

camphor, citric acid, diazolidinyl urea, hypromellose, methylparaben, propylene glycol, propylparaben, purified water, SD alcohol 40-B, sodium citrate

Distributed by:

SELECT BRAND DISTRIBUTORS

Pine Bluff, AR 71603 USA

AC (870) 535-3635

PACKAGE LABEL

FOR SKIN USE ONLY

SELECT BRAND

Topical Analgesic

ITCH STOPPING GEL

EXTRA STRENGTH

Diphenhydramine Hydrochloride 2%

4 FL OZ (118mL)